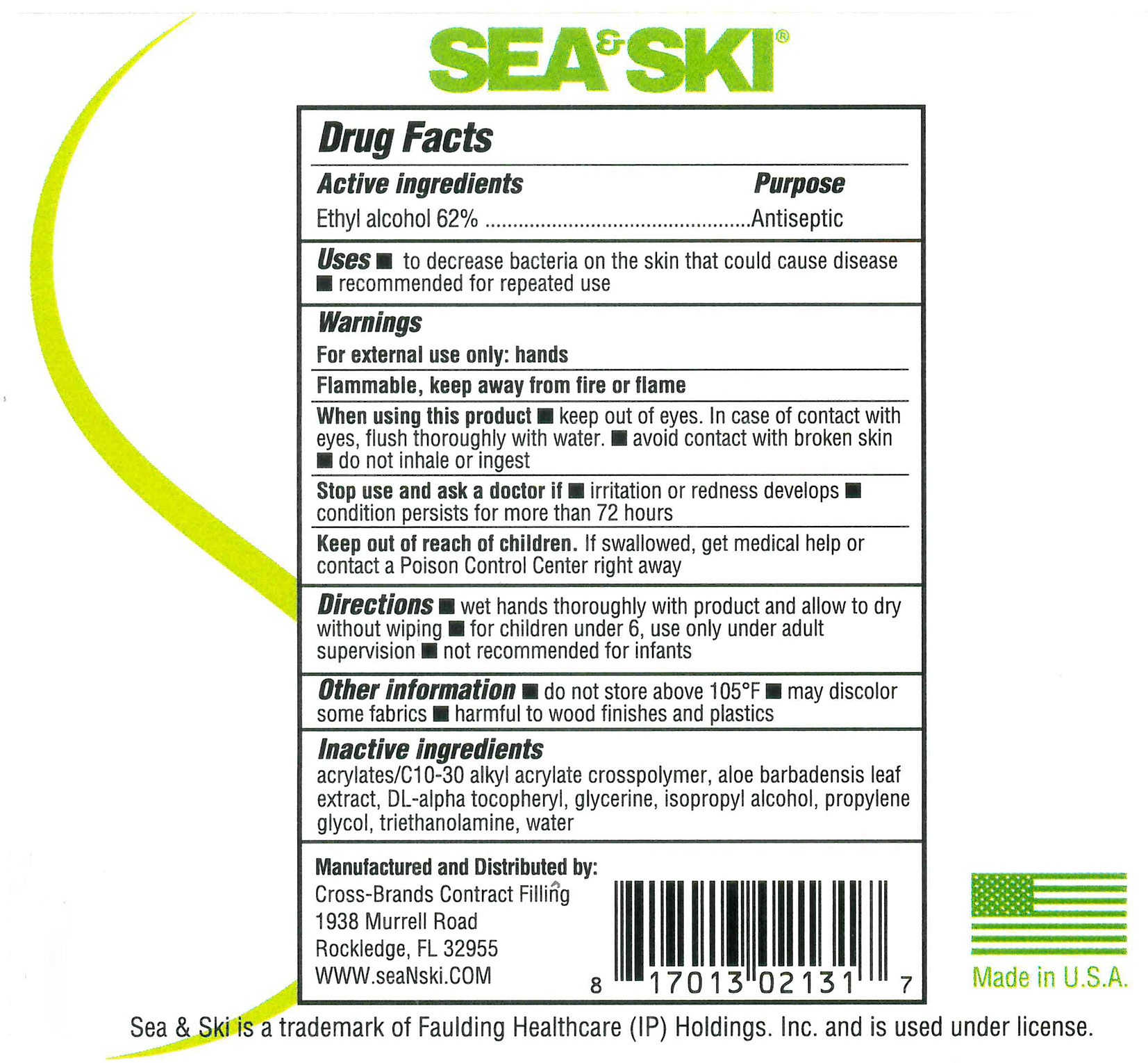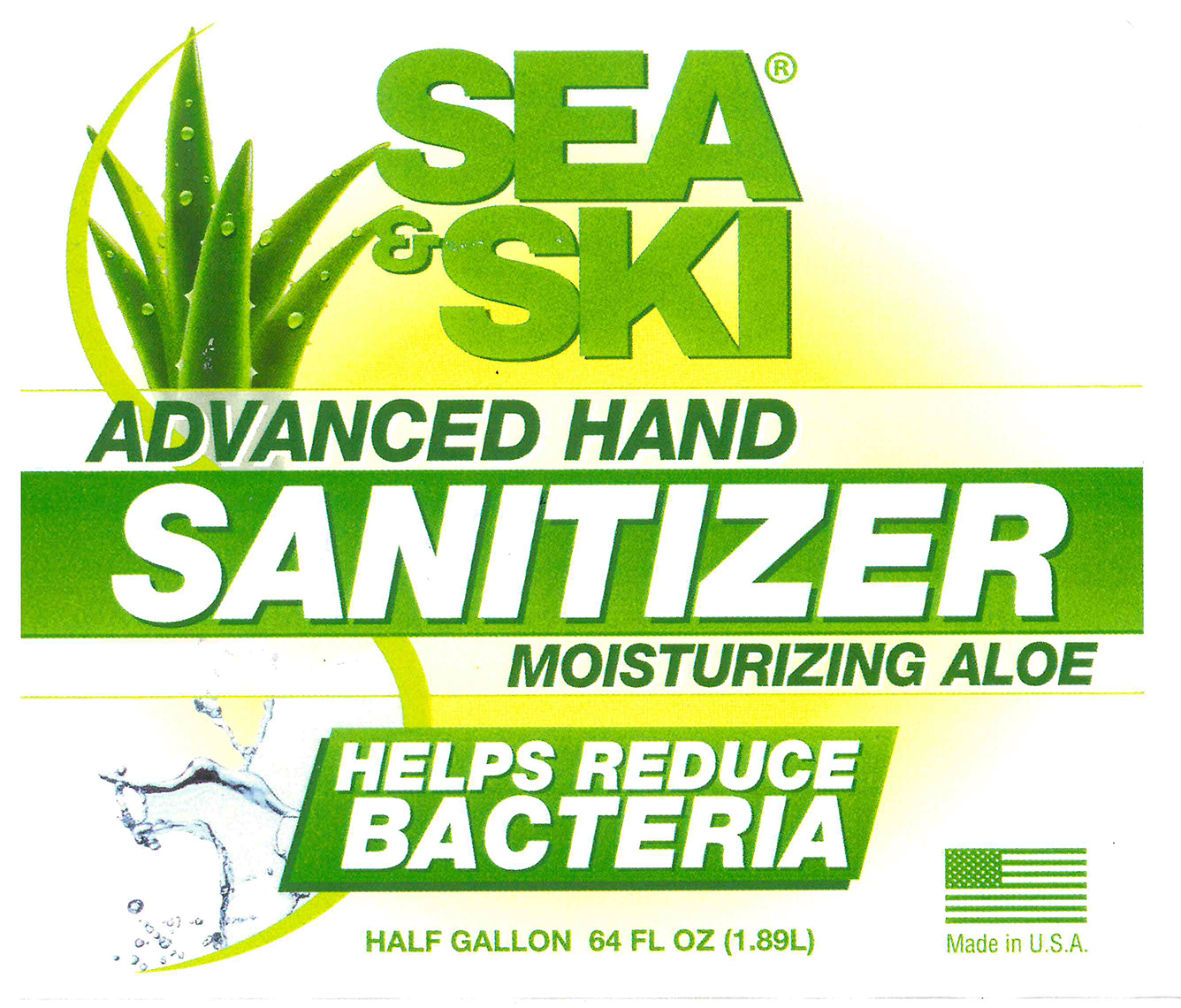 DRUG LABEL: Sea and Ski Advanced Hand Sanitizer
NDC: 73440-2131 | Form: GEL
Manufacturer: Cross-Brands Contract FIlling
Category: otc | Type: HUMAN OTC DRUG LABEL
Date: 20210219

ACTIVE INGREDIENTS: ALCOHOL 1124.91 g/1814.37 g
INACTIVE INGREDIENTS: WATER 489.34 g/1814.37 g

Sea&Ski Advanced Hand Sanitizer 64oz